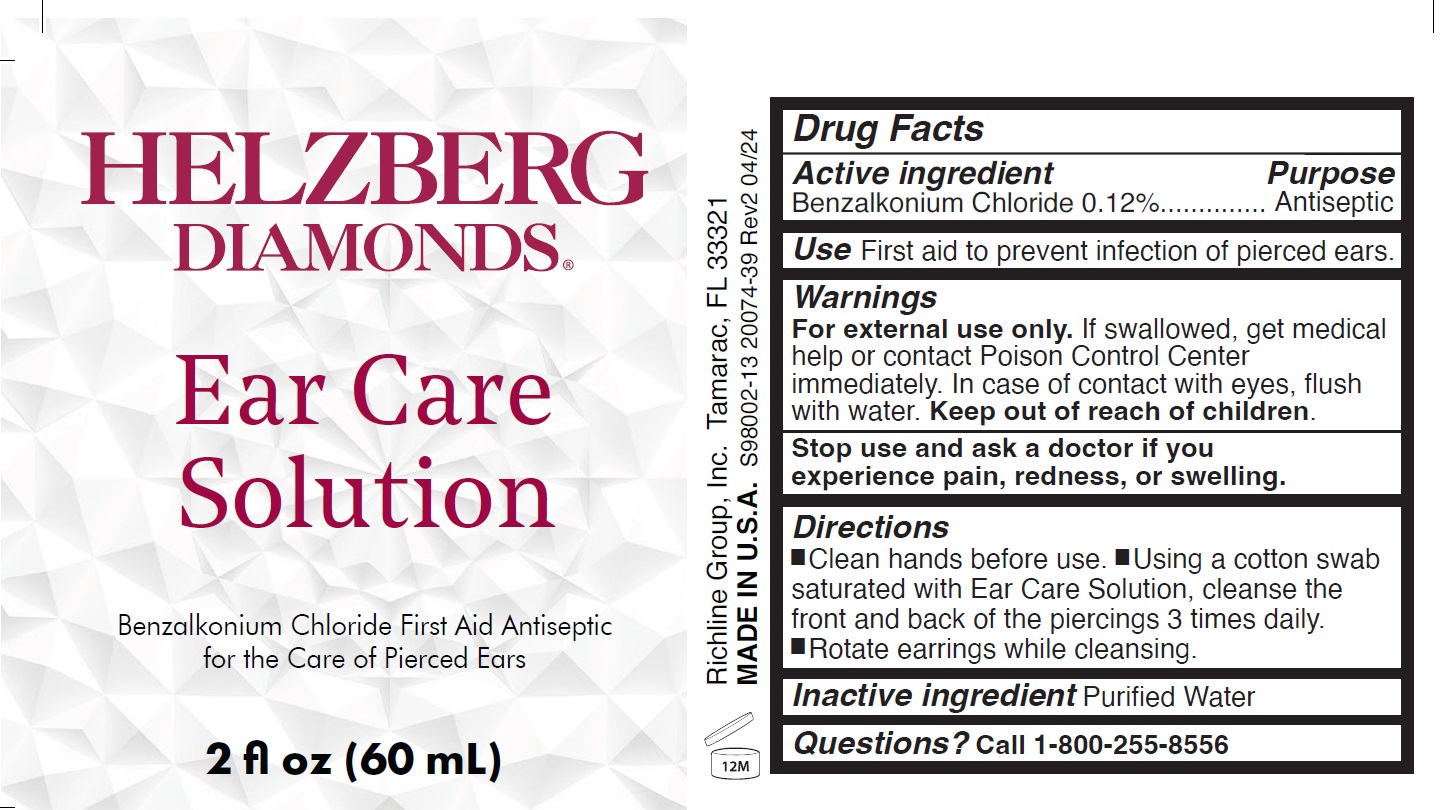 DRUG LABEL: Helzberg Diamonds Ear Care
NDC: 70094-008 | Form: SOLUTION
Manufacturer: The Richline Group, Inc.
Category: otc | Type: HUMAN OTC DRUG LABEL
Date: 20240509

ACTIVE INGREDIENTS: BENZALKONIUM CHLORIDE 1.2 mg/1 mL
INACTIVE INGREDIENTS: WATER

Helzberg Diamonds Ear Care Solution

Active ingredient

Benzalkonium Chloride 0.12% w/w

Purpose

Antiseptic

Use

First aid to prevent infection of pierced ears.

Warnings

For external use only. If swallowed, get medical help or contact Poison Control Center immediately. In case of contact with eyes, flush with water.

Stop use and ask a doctor if

you experience pain, redness, or swelling.

Directions

- Clean hands before use.
- Using a cotton swab saturated with Ear Care solution, cleanse front and back of the piercing 3 time daily.
- Rotate the earrings while cleasnsing.

Inactive ingredient

Purified Water

Questions?

Call1-800-255-8556